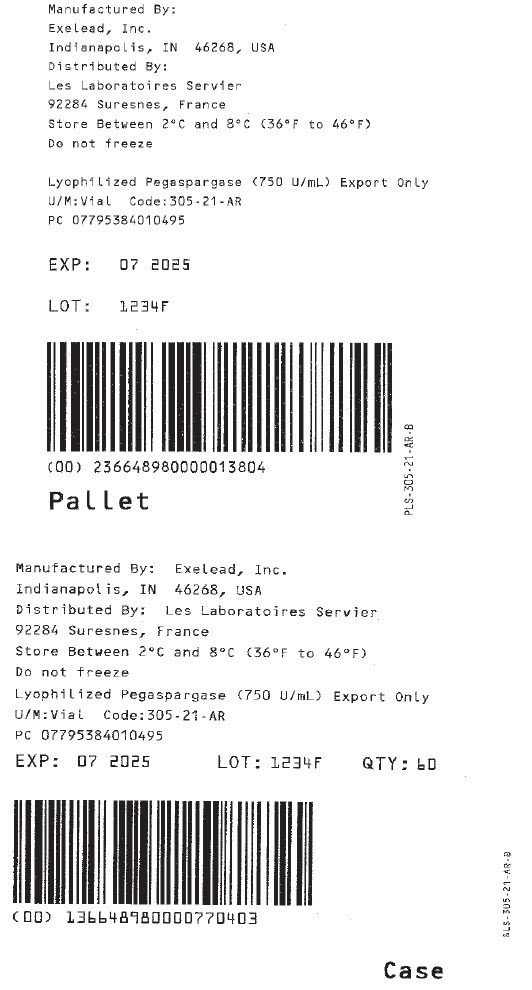 DRUG LABEL: LYOPHILIZED PEGASPARGASE
NDC: 72694-313 | Form: INJECTION, POWDER, LYOPHILIZED, FOR SOLUTION
Manufacturer: Servier Pharmaceuticals
Category: prescription | Type: HUMAN PRESCRIPTION DRUG LABEL
Date: 20200803

ACTIVE INGREDIENTS: PEGASPARGASE 750 [iU]/1 mL
INACTIVE INGREDIENTS: SODIUM PHOSPHATE, DIBASIC, UNSPECIFIED FORM; SODIUM PHOSPHATE, MONOBASIC, DIHYDRATE; SODIUM CHLORIDE; SUCROSE; SODIUM HYDROXIDE; HYDROCHLORIC ACID

Lyophilized Pegaspargase (750 U/mL) Export Only

PRINCIPAL DISPLAY PANEL - Shipping Label

Manufactured By:
Exelead, Inc.
Indianapolis, IN 46268, USA
Distributed By:
Les Laboratoires Servier
92284 Suresnes, France
Store Between 2°C and 8°C (36°F to 46°F)
Do not freeze

Lyophilized Pegaspargase (750 U/mL) Export Only
U/M:Vial
Code:305-21-AR
PC 07795384010495

EXP: 07 2025

LOT: 1234F

Pallet

PLS-305-21-AR-B

Manufactured By: Exelead, Inc.
Indianapolis, IN 46268, USA
Distributed By: Les Laboratoires Servier
92284 Suresnes, France
Store Between 2°C and 8°C (36°F to 46°F)
Do not freeze
Lyophilized Pegaspargase (750 U/mL) Export Only
U/M:Vial
Code:305-21-AR
PC 07795384010495

EXP: 07 2025
LOT: 1234F
QTY: 60

Case

ALS-305-21-AR-B